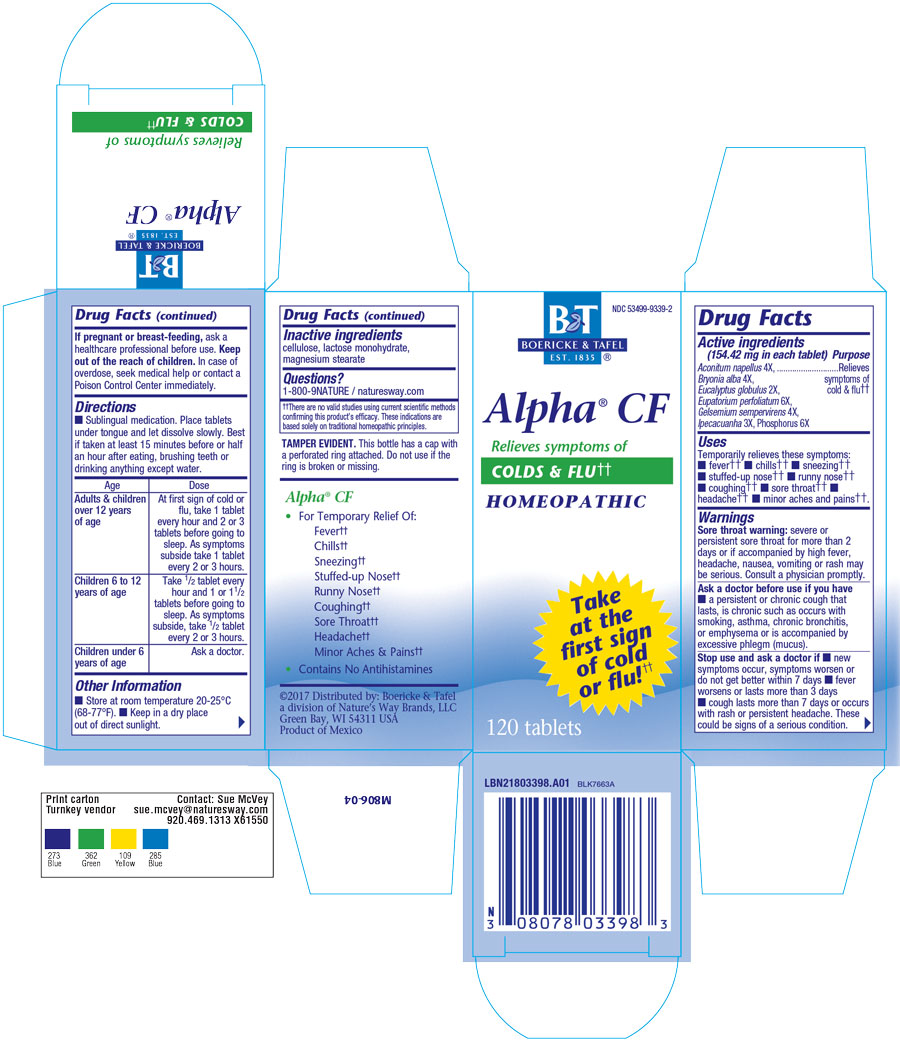 DRUG LABEL: ALPHA CF
NDC: 68466-3398 | Form: TABLET
Manufacturer: Schwabe Mexico, S.A. de C.V.
Category: homeopathic | Type: HUMAN OTC DRUG LABEL
Date: 20220503

ACTIVE INGREDIENTS: ACONITUM NAPELLUS 4 [hp_X]/1 1; BRYONIA ALBA ROOT 4 [hp_X]/1 1; EUPATORIUM PERFOLIATUM FLOWERING TOP 6 [hp_X]/1 1; GELSEMIUM SEMPERVIRENS ROOT 4 [hp_X]/1 1; IPECAC 3 [hp_X]/1 1; EUCALYPTUS GLOBULUS LEAF 2 [hp_X]/1 1; PHOSPHORUS 6 [hp_X]/1 1
INACTIVE INGREDIENTS: CELLULOSE, MICROCRYSTALLINE; LACTOSE MONOHYDRATE; MAGNESIUM STEARATE

Alpha CF Cold and Flu Tablets

Active Ingredients

Aconitum napellus 4X

Bryonia alba 4X

Eucalyptus globulus 2X

Eupatorium perfoliatum 6X

Gelsemium sempervirens 4X

Ipecacuanha 3X

Phosphorus 6X

Inactive Ingredient

Cellulose

Lactose monohydrate
Magnesium stearate

Dosage & Administration

Directions: Sublingual medication.

Place tablet under tongue and let dissolve slowly.

Best if taken at least 15 minutes before and a half hour after eating, brushing teeth, or drinking anything except water.

Adults and children 12 years of age and older:

At first sign of cold or flu, take 1 tablet every hour and 2 or 3 tablets before going to sleep.

As symptoms subside, take 1 tablet every 2 or 3 hours.

Children 6 to 12 years of age:

Take 1/2 tablet every hour and 1 or 1 1/2 tablets before going to sleep.
As symptoms subside, take 1/2 tablet every 2 or 3 hours.

Children under 2:

Ask a doctor

Purpose

Uses: Temporarily relieves these symptoms: fever, chills, sneezing, stuffed-up nose, runny nose, coughing, sore throat, headache, minor aches and pains.

Indication & Usage

Uses: Temporarily relieves these symptoms: fever, chills, sneezing, stuffed-up nose, runny nose, coughing, sore throat, headache, minor aches and pains.

Warning

Sore Throat Warning: severe or persistent sore throat for more that 2 days or if accompanied by high fever, headache, nausea, vomiting or rash may be serious.

Consult a physician promptly.

Ask doctor

Ask a Doctor before use if you have a persistent or chronic cough that lasts, is chronic such as occurs with smoking, asthma, chronic bronchitis, or emphysema or is accompanied by excessive phlegm (mucus).

Stop Use

Stop use and ask a doctor if new symptoms occur, symptoms worsen or do not get better within 7 days, fever worsens or lasts more than 3 days, cough lasts more than 7 days or occurs with rash or persisitent headache.
These could be signs of a serious condition.

Pregnancy or Breast Feeding

If pregnant or breast-feeding, ask a healthcare professional before use.

Keep out of reach of children

Keep out of the reach of children.

Overdosage

In case of overdose, seek medical help or contact a Poison Control Center immediately.